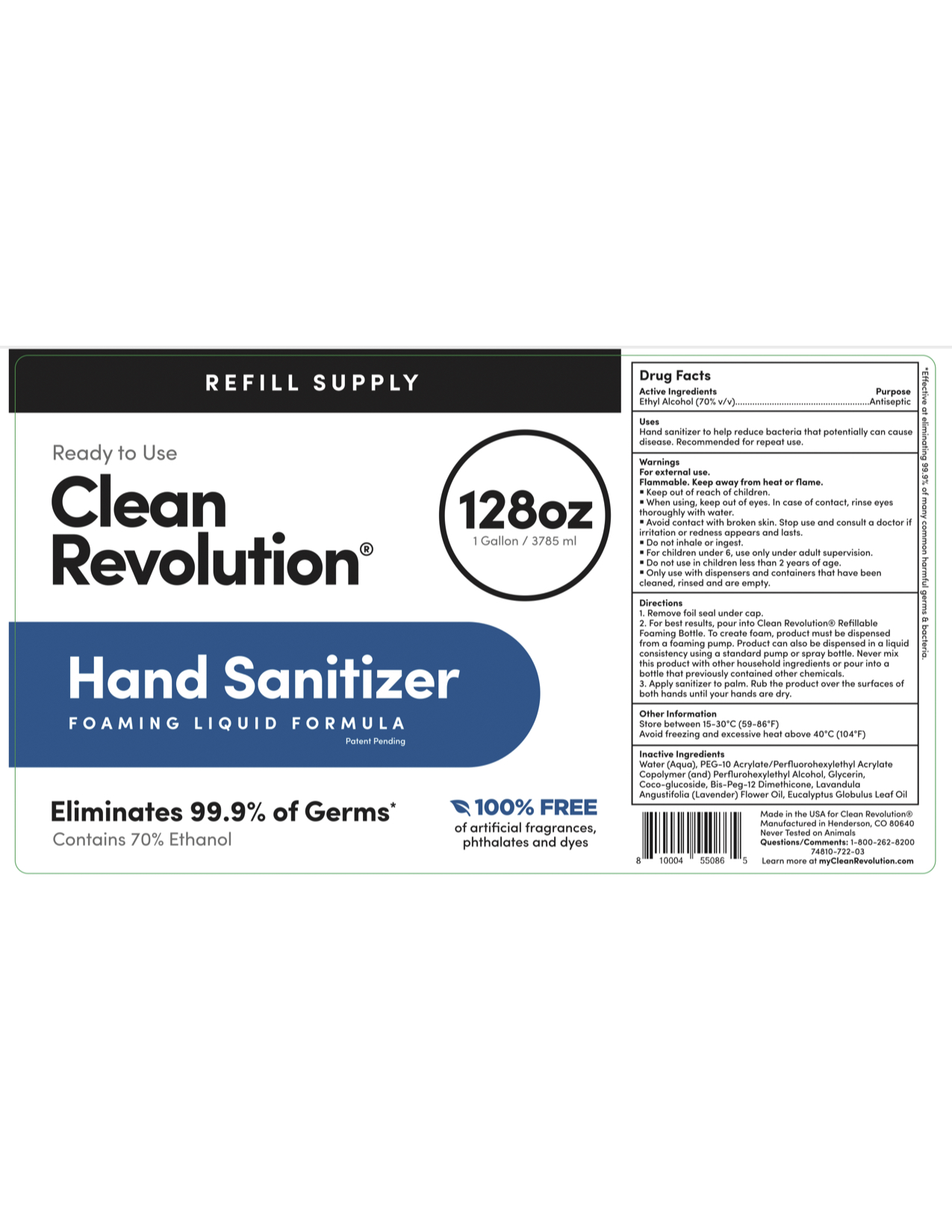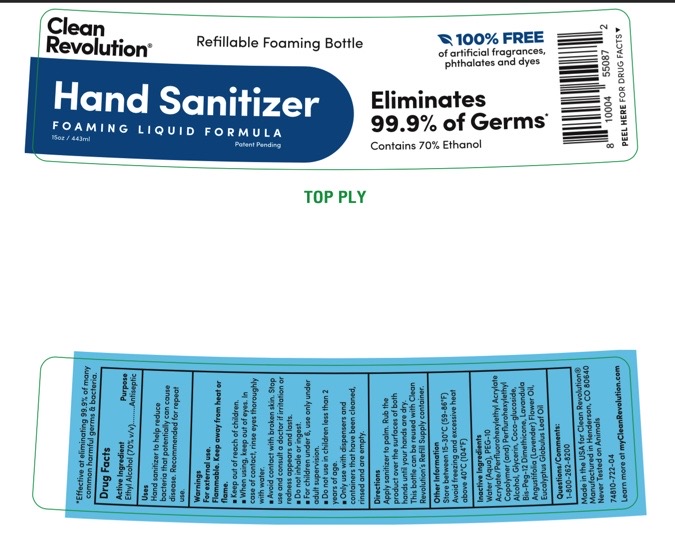 DRUG LABEL: Clean Revolution
NDC: 74810-722 | Form: LIQUID
Manufacturer: Replenish Bottling LLC
Category: otc | Type: HUMAN OTC DRUG LABEL
Date: 20200701

ACTIVE INGREDIENTS: ALCOHOL 65.3 g/100 g
INACTIVE INGREDIENTS: LAVENDER OIL 0.2 g/100 g; DECYL GLUCOSIDE 0.01 g/100 g; GLYCERIN 2 g/100 g; WATER 28.289 g/100 g; BIS-PEG-12 DIMETHICONE (500 MPA.S) 0.001 g/100 g; PEG-10 ACRYLATE/PERFLUOROHEXYLETHYL ACRYLATE COPOLYMER 4 g/100 g; EUCALYPTUS OIL 0.2 g/100 g

Active Ingredients.... Purpose

Ethyl Alcohol (70% v/v)..... Antiseptic

Purpose

Antiseptic

Uses

Hand sanitizer to help reduce bacteria that potentially can cause disease. Recommended for repeat use.

Warnings

For external use.

Flammable . Keep away from heat or flame.

Warnings

• Keep out of reach of children.

Warnings

• Avoid contact with broken skin. Stop use and consult a doctor if irritation or redness appears and lasts.

Warnings

When using, keep out of eyes. In case of contact, rinse eyes thoroughly with water.

Warnings

Avoid contact with broken skin. Stop use and consult a doctor if irritation or redness appears and lasts.

Warnings

• Do not inhale or ingest.

■ For children under 6, use only under adult supervision .

■ Do not use in children less than 2 years of age.

Warnings

■ Only use with dispensers and containers that have been cleaned, rinsed and are empty.

Directions

1. Remove foil seal under cap.

2. For best results , pour into Clean Revolution® Refillable Foaming Bottle. To create foam, product must be dispensed from a foaming pump. Product can also be dispensed in a liquid consistency using a standard pump or spray bottle. Never mix this product with other household ingredients or pour into a bottle that previously contained other chemicals.

3. Apply sanitizer to palm. Rub the product over the surfaces of both hands until your hands are dry.

Other Information

Store between 15-30 °C (59-86 °F)

Avoid freezing and excessive heat above 40°C (104°F)

Inactive Ingredients

Water (Aqua) , PEG-10 Acrylate/Perfluorohexylethyl Acrylate Copolymer (and) Perflurohexylethyl Alcohol, Glycerin, Coco-glucoside, Bis-Peg-12 Dimethicone, Lavandula Angustifolia (Lavender) Flower Oil, Eucalyptus Globulus Leaf Oil

PACKAGE LABEL

3785ml NDC 74810-722-03

443ml NDC 74810-722-04